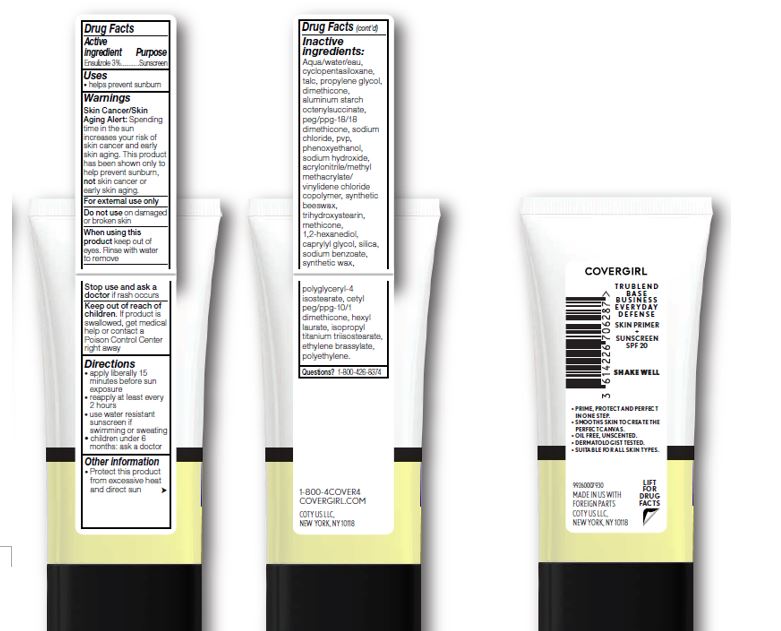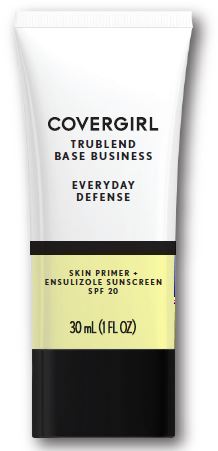 DRUG LABEL: Covergirl TruBlend Base Business Everyday Defense Primer SPF 20
NDC: 22700-157 | Form: LIQUID
Manufacturer: NOXELL CORPORATION
Category: otc | Type: HUMAN OTC DRUG LABEL
Date: 20241120

ACTIVE INGREDIENTS: ENSULIZOLE 3 g/100 mL
INACTIVE INGREDIENTS: WATER; PHENOXYETHANOL; SODIUM BENZOATE; ETHYLENE BRASSYLATE; TALC; SODIUM CHLORIDE; ALUMINUM STARCH OCTENYLSUCCINATE; HEXYL LAURATE; DIMETHICONE; TRIHYDROXYSTEARIN; 1,2-HEXANEDIOL; CAPRYLYL GLYCOL

Covergirl Everyday Defense Skin Primer SPF 20

Active ingredient

Ensulizole 3%

Purpose

Sunscreen

Uses

helps prevent sunburn

Warnings

Skin Cancer/Skin Aging Alert; Spending time in the sun increases your risk of skin cancer and early skin aging. This product has been shown only to help prevent sunburn, not skin cancer or early skin aging.

For external use only.

Do not use

on damaged or broken skin.

When using this product

keep out of eyes. Rinse with water to remove.

Stop use and ask a doctor

if rash occurs.

Keep out of reach of children.

If product is swallowed, get medical help or contact a Poison Control Center right away.

Directions

apply liberally 15 minutes before sun exposure

reapply at least every 2 hours

use a water resistant sunscreen if swimming or sweating
children under 6 months of age: Ask a doctor

Other information

protect this product from excessive heat and direct sun

INACTIVE INGREDIENT

Aqua/Water/Eau, Cyclopentasiloxane, Talc, Propylene Glycol, Dimethicone, Aluminum Starch Octenylsuccinate, PEG/PPG-18/18 Dimethicone, Sodium Chloride, PVP, Phenoxyethanol, Sodium Hydroxide, Ethylene/Methacrylate Copolymer, Synthetic Beeswax, Trihydroxystearin, Methicone, 1,2-Hexanediol, Caprylyl Glycol, Silica, Sodium Benzoate, Synthetic Wax, Polyglyceryl-4 Isostearate, Cetyl PEG/PPG-10/1 Dimethicone, Hexyl Laurate, Isopropyl Titanium Triisostearate, Ethylene Brassylate, Polyethylene.

Questions?

1-800-426-8374

PACKAGE LABEL

COVERGIRL

TRUBLEND

BASE BUSINESS

EVERYDAY

DEFENSE

SKIN PRIMER +

ENSULIZOLE SUNSCREEN

SPF 20

30 mL (1 FL OZ)